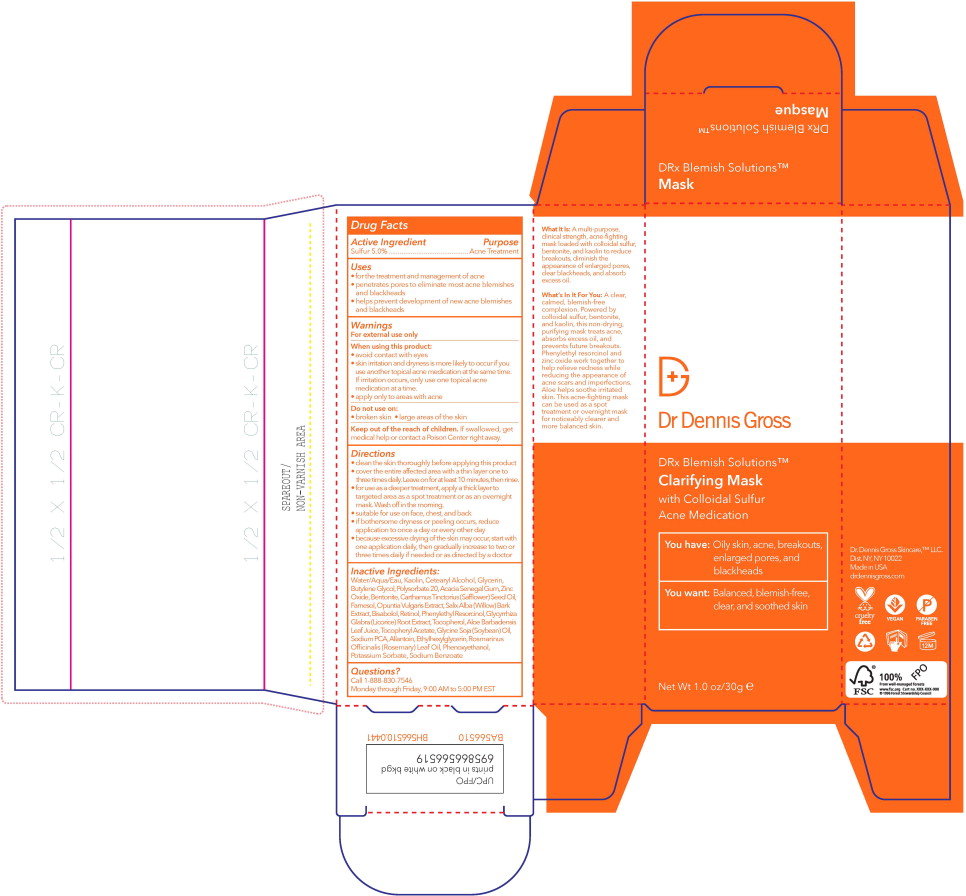 DRUG LABEL: DRx Blemish Clarifying Mask
NDC: 58633-704 | Form: LOTION
Manufacturer: Dr. Dennis Gross Skincare
Category: otc | Type: HUMAN OTC DRUG LABEL
Date: 20251215

ACTIVE INGREDIENTS: SULFUR 50 mg/1 mL
INACTIVE INGREDIENTS: WATER; KAOLIN; CETOSTEARYL ALCOHOL; BUTYLENE GLYCOL; GLYCERIN; POLYSORBATE 60; ACACIA; ZINC OXIDE; BENTONITE; SAFFLOWER OIL; PHENOXYETHANOL; LEVOMENOL; ALLANTOIN; ROSEMARY OIL; ALOE VERA LEAF; PHENYLETHYL RESORCINOL; SODIUM PYRROLIDONE CARBOXYLATE; .ALPHA.-TOCOPHEROL ACETATE; ETHYLHEXYLGLYCERIN; SOYBEAN OIL; OPUNTIA FICUS-INDICA WHOLE; FARNESOL; GLYCYRRHIZA GLABRA; SALIX ALBA BARK; RETINOL; CITRIC ACID MONOHYDRATE; POTASSIUM SORBATE; SODIUM BENZOATE

Drug Facts

Active Ingredient

Sulfur 5.0% ...........................................

Purpose

Acne Treatment

Uses

- for the treatment and management of acne
- penetrates pores to eliminate most acne blemishes and blackheads
- helps prevent development of new acne blemishes and blackheads

Warnings

For external use only

When using this product:

- avoid contact with eyes
- skin irritation and dryness is more likely to occur if you use another topical acne medication at the same time. If irritation occurs, only use one topical acne medication at a time.
- apply only to areas with acne

Do not use on:

- broken skin
- large areas of the skin

KEEP OUT OF REACH OF CHILDREN

Keep out of the reach of children.If swallowed, get medical help or contact a Poison Center right away.

Directions

- clean the skin thoroughly before applying this product
- cover the entire affected area with a thin layer one to three times daily. Leave on for at least 10 minutes, then rinse.
- for use as a deeper treatment, apply a thick layer to targeted area as a spot treatment or as an overnight mask. Wash off in the morning.
- suitable for use on face, chest, and back
- if bothersome dryness or peeling occurs, reduce application to once a day or every other day
- because excessive drying of the skin may occur, start with one application daily, then gradually increase to two or three times daily if needed or as directed by a doctor

Inactive Ingredients:

Water/Aqua/Eau, Kaolin, Cetearyl Alcohol, Glycerin, Butylene Glycol, Polysorbate 20, Acacia Senegal Gum, Zinc Oxide, Bentonite, Carthamus Tinctorius (Safflower) Seed Oil, Farnesol, Opuntia Vulgaris Extract, Salix Alba (Willow) Bark Extract, Bisabolol, Retinol, Phenylethyl Resorcinol, Glycyrrhiza Glabra (Licorice) Root Extract, Tocopherol, Aloe Barbadensis LeafJuice, Tocopheryl Acetate, Glycine Soja (Soybean) Oil, Sodium PCA, Allantoin, Ethylhexylglycerin, Rosmarinus Officinalis (Rosemary) Leaf Oil, Phenoxyethanol, Potassium Sorbate, Sodium Benzoate

Questions?

Call 1-888-830-7546

Monday through Friday, 9:00 AM to 5:00 PM EST

Principal Display Panel – 30 mL Box Label

Dr Dennis Gross

DRx Blemish Solutions™

Clarifying Mask
with Colloidal Sulfur
Acne Medication

You have:Oily skin, acne, breakouts,
enlarged pores, and
blackheads

You want:Balanced, blemish-free,
clear, and soothed skin

Net Wt 1.0 oz/30g ℮